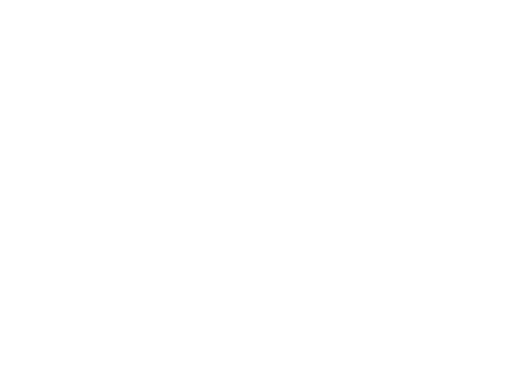 DRUG LABEL: Dorzolamide hydrochloride
NDC: 55545-1008 | Form: SOLUTION
Manufacturer: FDC Limited
Category: prescription | Type: HUMAN PRESCRIPTION DRUG LABEL
Date: 20191115

ACTIVE INGREDIENTS: DORZOLAMIDE HYDROCHLORIDE 20 mg/1 mL
INACTIVE INGREDIENTS: HYDROXYETHYL CELLULOSE (2000 MPA.S AT 1%); HYDROXYETHYL CELLULOSE (4000 MPA.S AT 1%); MANNITOL; SODIUM CITRATE; BENZALKONIUM CHLORIDE; SODIUM HYDROXIDE; WATER

Dorzolamide hydrochloride Ophthalmic Solution